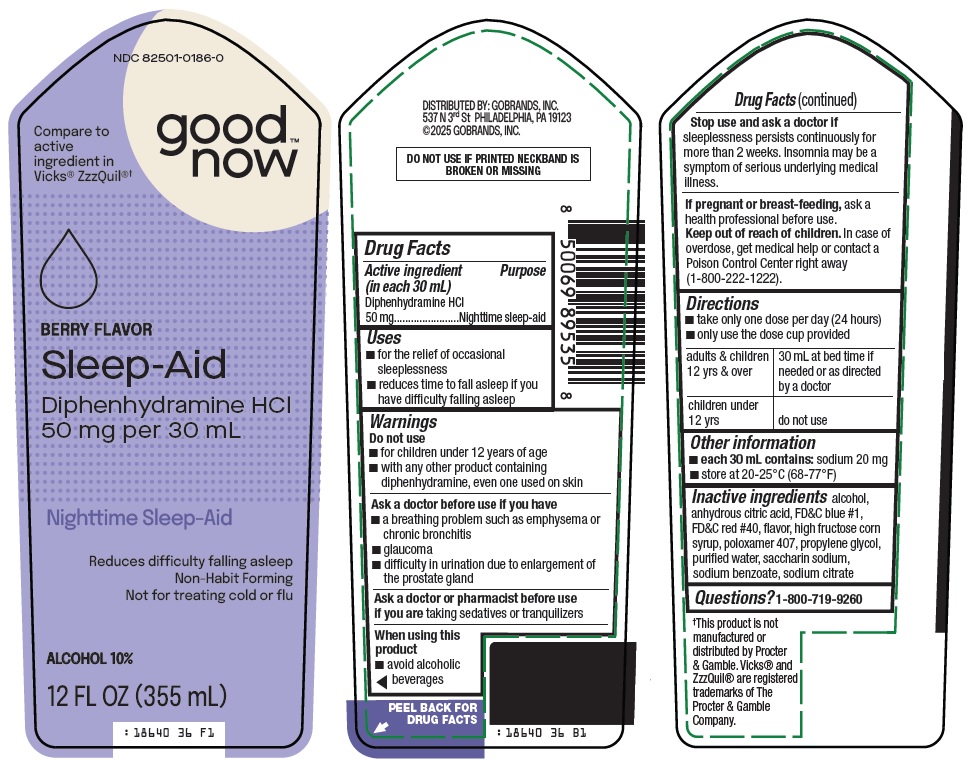 DRUG LABEL: GOODNOW SLEEP AID
NDC: 82501-0186 | Form: SOLUTION
Manufacturer: Gobrands, Inc
Category: otc | Type: HUMAN OTC DRUG LABEL
Date: 20251029

ACTIVE INGREDIENTS: DIPHENHYDRAMINE HYDROCHLORIDE 50 mg/30 mL
INACTIVE INGREDIENTS: ALCOHOL; ANHYDROUS CITRIC ACID; FD&C BLUE NO. 1; FD&C RED NO. 40; HIGH FRUCTOSE CORN SYRUP; POLOXAMER 407; PROPYLENE GLYCOL; WATER; SACCHARIN SODIUM; SODIUM BENZOATE; SODIUM CITRATE, UNSPECIFIED FORM

Gobrands, Inc. Sleep-Aid Drug Facts

Active ingredient (in each 30 mL)

Diphenhydramine HCl 50 mg

Purpose

Nighttime sleep-aid

Uses

- for the relief of occasional sleeplessness
- reduces time to fall asleep if you have difficulty falling asleep

Warnings

Do not use

- for children under 12 years of age
- with any other product containing diphenhydramine, even one used on skin

Ask a doctor before use if you have

- a breathing problem such as emphysema or chronic bronchitis
- glaucoma
- difficulty in urination due to enlargement of the prostate gland

Ask a doctor or pharmacist before use if you are

taking sedatives or tranquilizers

When using this product

- avoid alcoholic beverages

Stop use and ask a doctor if

sleeplessness persists continuously for more than 2 weeks. Insomnia may be a symptom of serious underlying medical illness.

If pregnant or breast-feeding,

ask a health professional before use.

Directions

- take only one dose per day (24 hours)
- only use the dose cup provided

adults & children 12 yrs & over | 30 mL at bed time if needed or as directed by a doctor
children under 12 yrs | do not use

Other information

- each 30 mL contains: sodium 20 mg
- store at 20-25°C (68-77°F)

Inactive ingredients

alcohol, anhydrous citric acid, FD&C blue #1, FD&C red #40, flavor, high fructose corn syrup, poloxamer 407, propylene glycol, purified water, saccharin sodium, sodium benzoate, sodium citrate

Questions?

1-800-719-9260

Package/Label Principal Display Panel

good™ now

Compare to active ingredient in Vicks® ZzzQuil®

BERRY FLAVOR

Sleep-Aid

Diphenhydramine HCl 50 mg per 30 mL

Nighttime Sleep-Aid

Reduces difficulty falling asleep

Non-Habit Forming

Not for treating cold or flu

ALCOHOL 10%

12 FL OZ (355 mL)